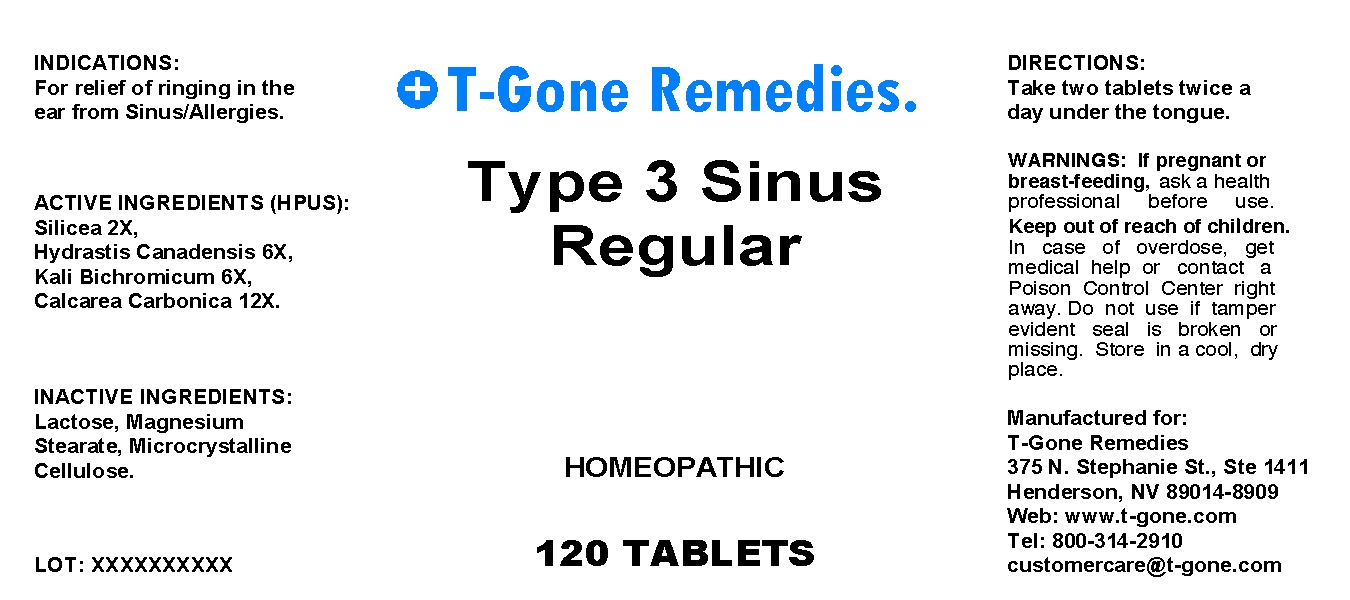 DRUG LABEL: Type 3 Sinus Regular
NDC: 57520-0425 | Form: TABLET
Manufacturer: Apotheca Company
Category: homeopathic | Type: HUMAN OTC DRUG LABEL
Date: 20100723

ACTIVE INGREDIENTS: SILICON DIOXIDE 2 [hp_X]/1 mg; GOLDENSEAL 6 [hp_X]/1 mg; POTASSIUM DICHROMATE 6 [hp_X]/1 mg; OYSTER SHELL CALCIUM CARBONATE, CRUDE 12 [hp_X]/1 mg
INACTIVE INGREDIENTS: LACTOSE; MAGNESIUM STEARATE; CELLULOSE, MICROCRYSTALLINE

Type 3 Sinus Regular

ACTIVE INGREDIENT

ACTIVE INGREDIENTS (HPUS): Silicea 2X, Hydrastis canadensis 6X, Kali bichromicum 6X, Calcarea carbonica 12X.

PURPOSE

INDICATIONS: For relief of ringing in the ear from Sinus/Allergies.

WARNINGS

WARNINGS: If pregnant or breast-feeding, ask a health professional before use.

Keep out of reach of children. In case of overdose, get medical help or contact a Poison Control Center right away.

Do not use if tamper evident seal is broken or missing. Store in a cool, dry place.

DOSAGE AND ADMINISTRATION

DIRECTIONS: Take two tablets twice a day under the tongue.

INACTIVE INGREDIENT

INACTIVE INGREDIENTS: Lactose, Magnesium stearate, Microcrystalline cellulose.

QUESTIONS

Manufactured for:
T-Gone Remedies
375 N. Stephanie St. Ste 1411
Henderson, NV 89014-8909
Web: www.t-gone.com
Tel: 800-314-2910
customercare@t-gone.com

PACKAGE LABEL

T-Gone Remedies

Type 3 Sinus Regular

HOMEOPATHIC

120 TABLETS